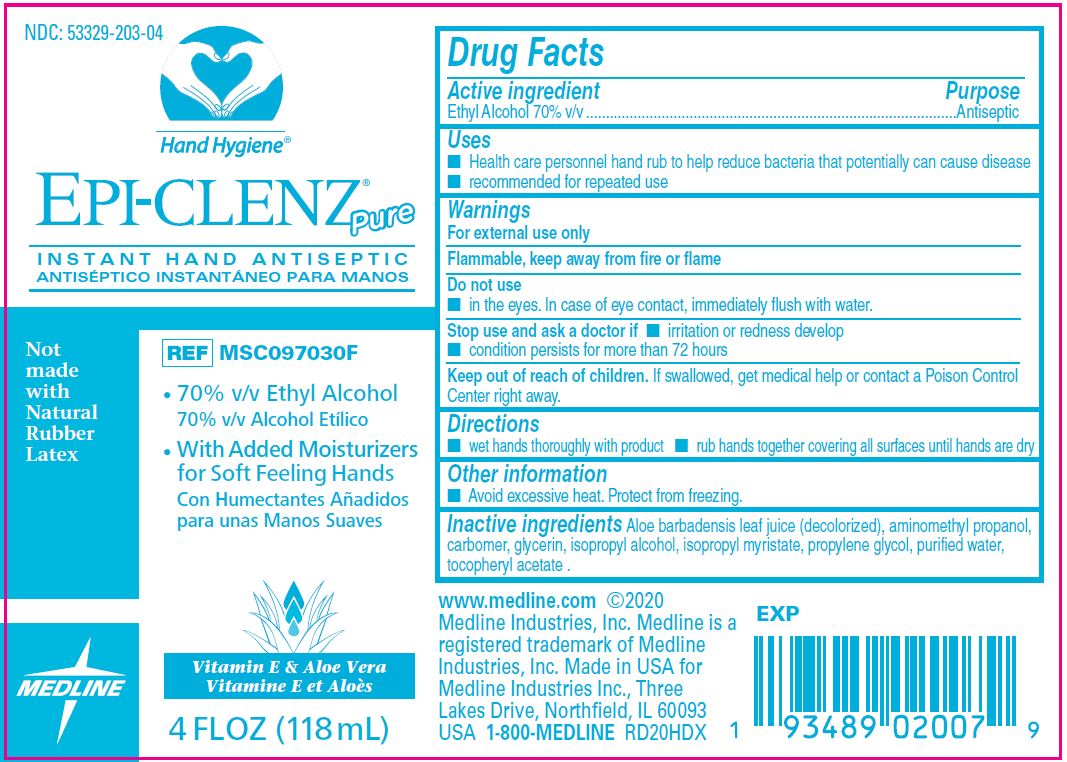 DRUG LABEL: Epi-Clenz Pure Instant Hand Antiseptic
NDC: 53329-203 | Form: GEL
Manufacturer: Medline Industries, LP
Category: otc | Type: HUMAN OTC DRUG LABEL
Date: 20260112

ACTIVE INGREDIENTS: ALCOHOL 70 mL/100 mL
INACTIVE INGREDIENTS: ALOE VERA LEAF; AMINOMETHYLPROPANOL; CARBOMER 934; GLYCERIN; ISOPROPYL ALCOHOL; ISOPROPYL MYRISTATE; PROPYLENE GLYCOL; .ALPHA.-TOCOPHEROL ACETATE, D-; WATER

203 Epi-Clenz Pure

Active ingredient

Ethyl Alcohol 70% v/v

Purpose

Antiseptic

Uses

- health care personnel hand rub to help reduce bacteria that potentially can cause disease
- recommended for repeated use

Warnings

For external use only.

Flammable, keep away from fire or flame.

Do not use

- in the eyes. In case of eye contact, immediately flush with water.

Stop use and ask a doctor if

- irritation or redness develop
- condition persists for more than 72 hours.

Keep out of reach of children.

If swallowed, get medical help or contact a Poison Control Center right away.

Directions

- wet hands thoroughly with product
- rub hands together covering all surfaces until hands are dry.

Other information

- Avoid excessive heat. Protect from freezing.

Inactive ingredients

Aloe barbadensis leaf juice, aminomethyl propanol, carbomer, glycerin, isopropyl alcohol, isopropyl myristate, propylene glycol, purified water, tocopheryl acetate